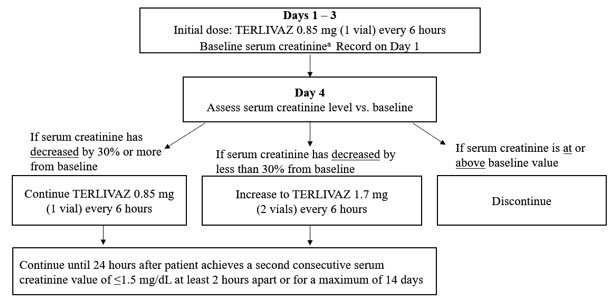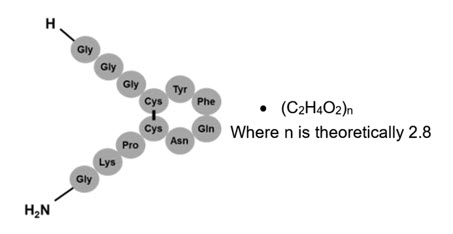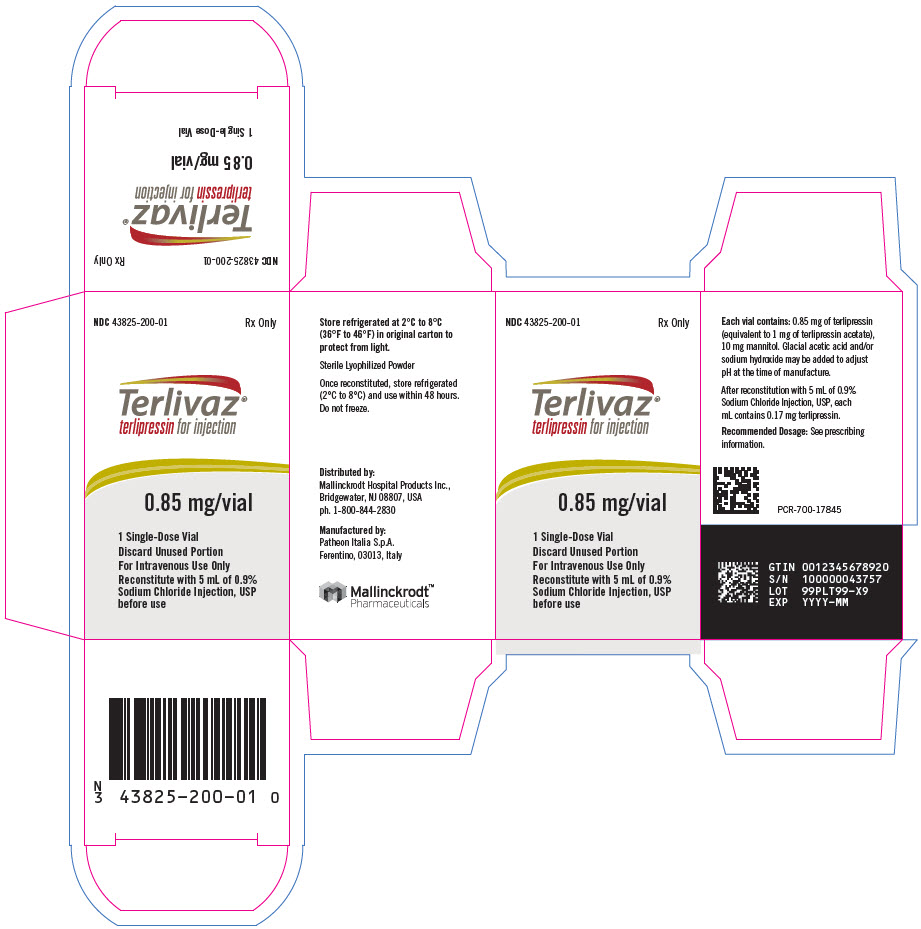 DRUG LABEL: Terlivaz
NDC: 43825-200 | Form: INJECTION, POWDER, LYOPHILIZED, FOR SOLUTION
Manufacturer: Mallinckrodt Hospital Products Inc.
Category: prescription | Type: HUMAN PRESCRIPTION DRUG LABEL
Date: 20251111

ACTIVE INGREDIENTS: TERLIPRESSIN 0.85 mg/5 mL

HIGHLIGHTS OF PRESCRIBING INFORMATION

These highlights do not include all the information needed to use TERLIVAZ® safely and effectively. See full prescribing information for TERLIVAZ.
TERLIVAZ (terlipressin) for injection, for intravenous use
Initial U.S. Approval: 2022

WARNING: SERIOUS OR FATAL RESPIRATORY FAILURE

TERLIVAZ may cause serious or fatal respiratory failure. Patients with volume overload or with ACLF Grade 3 are at increased risk. Assess oxygenation saturation (e.g., SpO2) before initiating TERLIVAZ.

Do not initiate TERLIVAZ in patients experiencing hypoxia (e.g., SpO2 <90%) until oxygenation levels improve. Monitor patients for hypoxia using continuous pulse oximetry during treatment and discontinue TERLIVAZ if SpO2 decreases below 90% (2.1, 4, 5.1).

1 INDICATIONS AND USAGE

TERLIVAZ is a vasopressin receptor agonist indicated to improve kidney function in adults with hepatorenal syndrome with rapid reduction in kidney function. (1)

Limitation of Use

Patients with a serum creatinine >5 mg/dL are unlikely to experience benefit. (1)

2 DOSAGE AND ADMINISTRATION

- Prior to initial dosing, assess patients for ACLF Grade 3 and obtain patient baseline oxygenation level. Monitor patient oxygen saturation with pulse oximetry. (2.1)
- Recommended Dosage Regimen: (2.2)
  - Days 1 to 3 administer TERLIVAZ 0.85 mg (1 vial) intravenously every 6 hours.
  - Day 4: Assess serum creatinine (SCr) versus baseline.
  - If SCr has decreased by at least 30% from baseline, continue TERLIVAZ 0.85 mg (1 vial) intravenously every 6 hours.
  - If SCr has decreased by less than 30% from baseline, dose may be increased to TERLIVAZ 1.7 mg (2 vials) intravenously every 6 hours.
  - If SCr is at or above baseline value, discontinue TERLIVAZ.
  - Continue TERLIVAZ until 24 hours after two consecutive SCr ≤1.5 mg/dL values at least 2 hours apart or a maximum of 14 days.
  See full prescribing information for instructions on preparation and administration (2.3). Flush IV line after administration.

3 DOSAGE FORMS AND STRENGTHS

For injection: TERLIVAZ 0.85 mg (1 vial) as a lyophilized powder in a single-dose vial for reconstitution. (3)

4 CONTRAINDICATIONS

TERLIVAZ is contraindicated:

In patients experiencing hypoxia or worsening respiratory symptoms. (4)
In patients with ongoing coronary, peripheral, or mesenteric ischemia. (4)

5 WARNINGS AND PRECAUTIONS

- Serious or Fatal Respiratory Failure: Monitor patients for changes in respiratory status using pulse oximetry and regular clinical assessments. Actively manage intravascular volume overload and adjust TERLIVAZ therapy as appropriate. (5.1)
- Ineligibility for Liver Transplant: TERLIVAZ-related adverse reactions may make a patient ineligible for liver transplantation, if listed. (5.2)
- Ischemic Events: TERLIVAZ is a vasoconstrictor and can cause ischemic events (cardiac, peripheral, or mesenteric) that may require dose interruption or discontinuation. (5.3)
- Embryo-Fetal Toxicity: TERLIVAZ may cause fetal harm when used during pregnancy. Advise females of reproductive potential of the potential hazard to the fetus. (5.4, 8.1)

6 ADVERSE REACTIONS

The most common adverse reactions (≥10%) include abdominal pain, nausea, respiratory failure, diarrhea, and dyspnea. (6.1)

To report SUSPECTED ADVERSE REACTIONS, contact 1-800-844-2830 and www.Mallinckrodt.com or FDA at 1-800-FDA-1088 or www.fda.gov/medwatch.

FULL PRESCRIBING INFORMATION

WARNING: SERIOUS OR FATAL RESPIRATORY FAILURE

TERLIVAZ may cause serious or fatal respiratory failure. Patients with volume overload or with acute-on-chronic liver failure (ACLF) Grade 3 are at increased risk [see References (15)]. Assess oxygenation saturation (e.g., SpO2) before initiating TERLIVAZ.

Do not initiate TERLIVAZ in patients experiencing hypoxia (e.g., SpO2 <90%) until oxygenation levels improve. Monitor patients for hypoxia using continuous pulse oximetry during treatment and discontinue TERLIVAZ if SpO2 decreases below 90% [see Dosage and Administration (2.1), Contraindications (4), and Warnings and Precautions (5.1)].

1 INDICATIONS AND USAGE

TERLIVAZ is indicated to improve kidney function in adults with hepatorenal syndrome with rapid reduction in kidney function.

Limitation of Use

Patients with a serum creatinine > 5 mg/dL are unlikely to experience benefit.

2 DOSAGE AND ADMINISTRATION

2.1 Important Considerations Prior to Initiating and During Therapy

Obtain baseline oxygen saturation (SpO2) prior to administering the first dose of TERLIVAZ. During treatment, monitor patient oxygen saturation using continuous pulse oximetry. Do not use TERLIVAZ treatment in patients experiencing hypoxia until hypoxia resolves [see Contraindications (4), and Warnings and Precautions (5.1)].

Assess Acute-on-Chronic Liver Failure (ACLF) Grade and volume status before initiating TERLIVAZ [see Warnings and Precautions (5.1) and References (15)].

2.2 Recommended Dosage

Record last available serum creatinine (SCr) value prior to initiating treatment (baseline SCr). The recommended starting dosage is TERLIVAZ 0.85 mg every 6 hours by slow intravenous bolus injection (over 2 minutes) on Days 1 through 3. Adjust the dose on Day 4 based on changes from baseline SCr using the dosing chart (Figure 1).

Figure 1: Dosing Chart

a Baseline SCr is the last available serum creatinine before initiating treatment.

2.3 Preparation and Administration

Reconstitute each vial with 5 mL of 0.9% Sodium Chloride Injection to prepare a 0.85 mg/5 mL solution. Parenteral drug products should be inspected visually for particulate matter and discoloration prior to administration, whenever solution and container permit.

Administer TERLIVAZ through a peripheral or central line. A dedicated central line is not required. Flush the line after TERLIVAZ administration.

If not administered immediately, store TERLIVAZ at 2°C to 8°C (36°F to 46°F) for up to 48 hours. Do not freeze. The reconstituted solution does not need protection from light.

3 DOSAGE FORMS AND STRENGTHS

For injection: TERLIVAZ 0.85 mg is a white to off-white lyophilized powder in a single-dose vial for reconstitution.

4 CONTRAINDICATIONS

TERLIVAZ is contraindicated in patients experiencing hypoxia or worsening respiratory symptoms.

TERLIVAZ is contraindicated in patients with ongoing coronary, peripheral or mesenteric ischemia.

5 WARNINGS AND PRECAUTIONS

5.1 Serious or Fatal Respiratory Failure

In the primary clinical trial [see Clinical Studies (14)], serious or fatal respiratory failure occurred in 14% of patients treated with TERLIVAZ compared to 5% of patients on placebo.

Obtain baseline oxygen saturation and do not initiate TERLIVAZ in hypoxic patients [see Contraindications (4)]. Monitor patients for changes in respiratory status using continuous pulse oximetry and regular clinical assessments. Discontinue TERLIVAZ in patients experiencing hypoxia or increased respiratory symptoms.

Patients with fluid overload may be at increased risk of respiratory failure. Manage intravascular volume overload by reducing or discontinuing the administration of albumin and/or other fluids and judicious use of diuretics. Temporarily interrupt, reduce, or discontinue TERLIVAZ treatment until patient volume status improves [see Dosage and Administration (2.1)].

Avoid use in patients with ACLF Grade 3 because they are at significant risk for respiratory failure [see References (15)].

5.2 Ineligibility for Liver Transplant

TERLIVAZ-related adverse reactions (respiratory failure, ischemia) may make a patient ineligible for liver transplantation, if listed. For patients with high prioritization for liver transplantation (e.g., MELD ≥ 35), the benefits of TERLIVAZ may not outweigh its risks [see Adverse Reactions (6.1)].

5.3 Ischemic Events

TERLIVAZ may cause cardiac, cerebrovascular, peripheral, or mesenteric ischemia. Avoid use of TERLIVAZ in patients with a history of severe cardiovascular conditions, cerebrovascular and ischemic disease. Discontinue TERLIVAZ in patients who experience signs or symptoms suggestive of ischemic adverse reactions [see Dosage and Administration (2.1) and Adverse Reactions (6.1)].

5.4 Embryo-Fetal Toxicity

TERLIVAZ may cause fetal harm when administered to a pregnant woman based on the mechanism of action and data from published literature. Terlipressin induces uterine contractions and endometrial ischemia in both humans and animals. If this drug is used during pregnancy, the patient should be apprised of the potential risk to the fetus [see Use in Specific Populations (8.1) and Clinical Pharmacology (12.1)].

6 ADVERSE REACTIONS

The following adverse reactions are discussed elsewhere in the labeling:

- Serious or Fatal Respiratory Failure [see Warnings and Precautions (5.1)]
- Ischemic Events [see Warnings and Precautions (5.3)]

6.1 Clinical Trials Experience

Because clinical trials are conducted under widely varying conditions, the adverse reaction rates observed in the clinical trials of TERLIVAZ cannot be directly compared to rates in the clinical trials of another drug and may not reflect the rates observed in practice.

The safety of TERLIVAZ was evaluated in the CONFIRM trial [see Clinical Studies (14)]. The average daily dose of TERLIVAZ was 3.1 mg (range 0.8 to 5.8 mg), with a mean duration of exposure to TERLIVAZ of 6.2 days (range 1 to 15 days).

Treatment discontinuation due to adverse events occurred in 12.0% (24/200) of patients receiving TERLIVAZ and 5.1% (5/99) of patients receiving placebo. The most common adverse reactions that led to TERLIVAZ discontinuation were respiratory failure, abdominal pain, and intestinal ischemia/obstruction.

Table 1 lists adverse reactions that occurred more commonly on TERLIVAZ than on placebo, and in at least 4% of patients treated with TERLIVAZ in the CONFIRM trial. The most commonly observed adverse reactions in TERLIVAZ-treated patients (≥10%) were abdominal pain, nausea, respiratory failure, diarrhea, and dyspnea.

Table 1: Adverse Reactions Reported by ≥4 % of TERLIVAZ-Treated Patients
 | Patients, n (%)
 | TERLIVAZ (N=200) | Placebo (N=99)
Abdominal pain | 39 (19.5) | 6 (6.1)
Nausea | 32 (16.0) | 10 (10.1)
Respiratory failure | 31 (15.5) | 7 (7.1)
Diarrhea | 26 (13.0) | 7 (7.1)
Dyspnea | 25 (12.5) | 5 (5.1)
Fluid overload | 17 (8.5) | 3 (3.0)
Pleural effusion | 11 (5.5) | 0 (0.0)
Sepsis | 11 (5.5) | 1 (1.0)
Bradycardia | 10 (5.0) | 0 (0.0)
Ischemia-related events [Ischemia-related events include: skin discoloration, cyanosis, ischemia and intestinal ischemia.] | 9 (4.5) | 0 (0.0)

6.2 Postmarketing Experience

Adverse reactions reported from the worldwide postmarketing experience with terlipressin include headache, hyponatremia, skin necrosis and gangrene. Because these reactions are reported voluntarily from a population of uncertain size, it is not always possible to reliably estimate their frequency or establish a causal relationship to terlipressin exposure.

8 USE IN SPECIFIC POPULATIONS

8.1 Pregnancy

Risk Summary

Based on findings from the published literature and on its mechanism of action, TERLIVAZ may cause fetal harm when administered to a pregnant woman [see Clinical Pharmacology (12.1)]. In small, published studies, administration of a single intravenous dose of terlipressin to pregnant women during the first trimester induced uterine contractions and endometrial ischemia. The limited published data are not sufficient to determine a drug-associated risk for major birth defects or miscarriage. If TERLIVAZ is used during pregnancy, the patient should be informed of the potential risk to the fetus.

The background risk of major birth defects and miscarriage for the indicated population is unknown. In the U.S. general population, the estimated background risk of major birth defects and miscarriage in clinically recognized pregnancies is 2% to 4% and 15% to 20%, respectively.

Data

Animal Data

In published reproductive toxicity animal studies, administration of terlipressin to pregnant guinea pigs at doses lower than the maximum recommended human dose of 4 mg/day caused a marked decrease in blood flow to the uterus and placenta. In rabbits, terlipressin is both embryotoxic and teratogenic (increased resorptions, increased implantation loss, fetal anomalies and fetal deformities).

8.2 Lactation

Risk Summary

There are no data on the presence of terlipressin in human or animal milk, the effects on the breastfed infant, or the effect on milk production. The developmental and health benefits of breastfeeding should be considered along with the mother's clinical need for TERLIVAZ and any potential adverse effects on the breastfed child from TERLIVAZ or from the underlying maternal condition.

8.4 Pediatric Use

Safety and effectiveness of TERLIVAZ have not been established in pediatric patients.

8.5 Geriatric Use

Of the total number of patients in clinical studies treated with TERLIVAZ, 55 (16%) were ≥65 years of age. No overall differences in safety or effectiveness were observed between these subjects and younger subjects; other reported clinical experience has not identified differences in responses between the elderly and younger patients, but greater sensitivity of some older individuals cannot be ruled out.

8.6 Hepatic Impairment

No dose adjustment is required in patients with hepatic impairment [see Clinical Pharmacology (12.3)].

10 OVERDOSAGE

Manifestations of TERLIVAZ overdose are expected to be similar to the adverse reactions described with therapeutic doses. In case of overdose, initiate close monitoring of vital signs, electrolytes, and potential ischemic events and initiate appropriate symptomatic treatment.

11 DESCRIPTION

TERLIVAZ contains terlipressin, a vasopressin receptor agonist. Terlipressin is a 12-amino acid peptide with the chemical name N-[N-(N-glycylglycyl)glycyl]-8-L-lysinevasopressin. The structure of terlipressin acetate is shown below:

Molecular formula: C52H74N16O15S2 ∙ (C2H4O2)n; (n=number of acetate molecules; theoretical n=2.8)

Average molecular weight: 1227.38 (as free base)

TERLIVAZ is supplied as a sterile, preservative-free, lyophilized, white-to off-white powder for intravenous administration. Each vial contains 0.85 mg terlipressin, equivalent to 1 mg terlipressin acetate, and 10.0 mg mannitol. Glacial acetic acid and/or sodium hydroxide may be added to adjust pH at the time of manufacture.

12 CLINICAL PHARMACOLOGY

12.1 Mechanism of Action

Terlipressin is a synthetic vasopressin analogue with twice the selectivity for vasopressin V1 receptors versus V2 receptors. Terlipressin acts as both a prodrug for lysine-vasopressin, as well as having pharmacologic activity on its own. Terlipressin is thought to increase renal blood flow in patients with hepatorenal syndrome by reducing portal hypertension and blood circulation in portal vessels and increasing effective arterial volume and mean arterial pressure (MAP).

12.2 Pharmacodynamics

After administration of a single 0.85 mg dose of terlipressin in patients with hepatorenal syndrome type 1 (HRS-1), an increase in the diastolic, systolic, and mean arterial pressure (MAP), and decrease in heart rate were evident within 5 minutes after dosing and were maintained for at least 6 hours after dosing. The maximum change in blood pressure and heart rate occurred at 1.2 to 2 hours post dose. For MAP, the estimated maximum effect was an increase of 16.2 mmHg. The estimated maximum effect for heart rate was a decrease of 10.6 beats/minute.

Cardiac Electrophysiology

The effect of terlipressin on QTc interval was evaluated in 41 patients with HRS-1. Patients received an initial dose of 1 mg terlipressin acetate every 6 hours for a period of up to 14 days. No clinically meaningful changes from baseline were detected in the trial based on the Fridericia correction method. Increases of the mean QTc interval of <10 ms were reported.

12.3 Pharmacokinetics

The pharmacokinetic parameters of terlipressin and its major active metabolite, lysine-vasopressin, were derived from population pharmacokinetic modeling with sparse PK samples from 69 patients with HRS-1.

Following a 1 mg IV injection of terlipressin acetate, the median Cmax, AUC24h and Cave of terlipressin at steady state was 70.5 ng/mL, 123 ng×hr/mL and 14.2 ng/mL, respectively. The median Cmax, AUC24h and Cave of lysine-vasopressin were 1.2 ng/mL, 11.2 ng×hr/mL and 0.5 ng/mL, respectively.

Terlipressin and lysine-vasopressin exhibit linear pharmacokinetics in healthy subjects. Plasma concentrations of terlipressin demonstrate proportional increases with the dose administered.

Distribution

The volume of distribution (Vd) of terlipressin was 6.3 L and 1370 L for lysine-vasopressin.

Elimination

The clearance of terlipressin was 27.4 L/hr and 318 L/hr for lysine-vasopressin. There were no dose-dependent changes in the elimination rate constant of terlipressin in healthy subjects. Clearance of terlipressin in HRS-1 patients increased with body weight, while body weight had no effect on the clearance of lysine-vasopressin.

The terminal half-life of terlipressin was 0.9 hours and 3.0 hours for lysine-vasopressin.

Metabolism

Terlipressin is metabolized by cleavage of the N-terminal glycyl residues of terlipressin by various tissue peptidases, resulting in release of the pharmacologically active metabolite lysine-vasopressin. Once formed, lysine-vasopressin is metabolized by body tissue via various peptidase-mediated routes. Terlipressin is not metabolized in blood or plasma. Due to the ubiquitous nature of peptidases in body tissue, it is unlikely that the metabolism of terlipressin will be affected by disease state or other drugs.

Excretion

Less than 1% of terlipressin and <0.1% of lysine-vasopressin is excreted in urine in healthy subjects.

Specific Populations

Gender, age, creatinine clearance, Child-Pugh score, serum alkaline phosphatase, serum alanine aminotransferase (ALT), serum aspartate aminotransferase (AST), and total bilirubin do not appear to have any clinically significant effect on clearance of either terlipressin or lysine-vasopressin.

Drug Interactions

In vitro studies in human liver microsomes demonstrated that there was little or no evidence that terlipressin was a direct-, time-, or metabolism-dependent inhibitor and inducer of any of the CYP enzymes evaluated. In addition, there was little or no evidence that terlipressin is an inhibitor and substrate of human ABC and SLC transporters. No significant drug-drug interactions are anticipated with TERLIVAZ.

13 NONCLINICAL TOXICOLOGY

13.1 Carcinogenesis, Mutagenesis, Impairment of Fertility

Carcinogenicity studies have not been performed with terlipressin.

Terlipressin was not mutagenic or clastogenic in the following tests: in vitro bacterial reverse mutation assay, in vivo mouse micronucleus assay, and in vitro mammalian cell (CHO) chromosome aberration assay.

No studies with terlipressin have been conducted in animals to evaluate its effect on fertility.

14 CLINICAL STUDIES

The efficacy of TERLIVAZ was assessed in a multicenter, double-blind, randomized, placebo-controlled study (CONFIRM) (NCT02770716). Patients with cirrhosis, ascites, and a diagnosis of HRS-1 with a rapidly progressive worsening in renal function to a serum creatinine (SCr) ≥2.25 mg/dL and meeting a trajectory for SCr to double over two weeks, and without sustained improvement in renal function (<20% decrease in SCr and SCr ≥2.25 mg/dL) 48 hours after both diuretic withdrawal and the beginning of plasma volume expansion with albumin were eligible to participate. All patients underwent fluid challenge with intravenous albumin (1 g/kg on the first day (maximum 100 g) and 20 g/day to 40 g/day thereafter as clinically indicated). Patients with a baseline serum creatinine level >7.0 mg/dL, shock, sepsis, and/or uncontrolled bacterial infection were excluded from the study. Use of vasopressors was prohibited during the treatment period.

A total of 300 patients were enrolled; the median age was 55 years (range: 23 to 82), 60% were male, and 90% were White. At baseline, 40% had alcoholic hepatitis and 19% had ACLF Grade 3; the mean serum creatinine was 3.5 mg/dL, and the mean MELD score was 33.

Patients were randomized 2:1 to treatment with TERLIVAZ (N=199) or placebo (N=101). Patients received 1 mg terlipressin acetate (equivalent to TERLIVAZ 0.85 mg) or placebo every 6 hours administered as an IV bolus injection over 2 minutes for a maximum of 14 days. On Day 4 of therapy, if SCr decreased by less than 30% from the baseline value, the dose was increased to 2 mg terlipressin acetate (equivalent to TERLIVAZ 1.7 mg) every 6 hours. If SCr was at or above the baseline value on Day 4, then treatment was discontinued. Both treatment groups received albumin therapy during the study (median dose 50 g/day). Concomitant diuretics were used in 26% of patients treated with TERLIVAZ and 13% of patients treated with placebo. Median treatment duration was 5 days for TERLIVAZ-treated patients and 4 days for placebo-treated patients.

The primary efficacy endpoint was the incidence of Verified HRS Reversal, defined as the percentage of patients with 2 consecutive SCr values of ≤1.5 mg/dL, obtained at least 2 hours apart while on treatment by Day 14 or discharge. To be included in the primary efficacy endpoint analysis, patients had to be alive and without intervening renal replacement therapy (e.g., dialysis) at least 10 days after achieving Verified HRS Reversal.

A greater proportion of patients achieved Verified HRS Reversal in the TERLIVAZ arm compared to the placebo arm (Table 2).

Table 2: Efficacy Analyses
 | TERLIVAZ N = 199 | Placebo N = 101 | P value
Verified HRS Reversal [Primary endpoint] , n (%) | 58 (29.1) | 16 (15.8) | 0.012
95% CI | (0.2, 0.4) | (0.1, 0.2)
Durability of HRS Reversal [Patients with a SCr value of not more than 1.5 mg/dL while on treatment, by Day 14, or discharge.] , [Patients with HRS Reversal without renal replacement therapy to Day 30.] , n (%) | 63 (31.7) | 16 (15.8) | 0.003
95% CI | (0.3, 0.4) | (0.1, 0.2)
Incidence of HRS Reversal in the Systemic Inflammatory Response Syndrome (SIRS) Subgroup, n (%) | N=84 28 (33.3) | N=48 3 (6.3) | <0.001
95% CI | (0.2, 0.4) | (0.0, 0.1)
Incidence of Verified HRS Reversal without HRS Recurrence by Day 30, n (%) | 48 (24.1) | 16 (15.8) | 0.092
95% CI | (0.2, 0.3) | (0.1, 0.2)
CI = confidence interval

15 REFERENCES

Jalan R, et al; Development and validation of a prognostic score to predict mortality in patients with acute-on-chronic liver failure. J Hepatol. 2014 Nov;61(5):1038-47.

16 HOW SUPPLIED/STORAGE AND HANDLING

TERLIVAZ is supplied as a sterile, preservative-free, white to off-white lyophilized powder in single-dose vials containing 0.85 mg of terlipressin. Each vial is supplied in a carton (NDC 43825-200-01).

STORAGE AND HANDLING

Store TERLIVAZ vials in the carton under refrigerated conditions at 2°C to 8°C (36°F to 46°F). Store in the original carton to protect from light prior to reconstitution.

17 PATIENT COUNSELING INFORMATION

Embryo-Fetal Toxicity

Inform female patients of reproductive potential that TERLIVAZ may cause fetal harm and to inform their prescriber of a known or suspected pregnancy [see Use in Specific Populations (8.1)].

Distributed by:
Mallinckrodt Hospital Products Inc.
Bridgewater, NJ 08807, USA

Mallinckrodt, the "M" brand mark and the Mallinckrodt Pharmaceuticals logo are trademarks of a Mallinckrodt company. Other brands are trademarks of a Mallinckrodt company or their respective owners. ©2023 Mallinckrodt.

For a list of patents, see https://www.mallinckrodt.com/patents/

Part # PCR-750-17846

PRINCIPAL DISPLAY PANEL - 0.85 mg Vial Carton

NDC 43825-200-01
Rx Only

Terlivaz®
terlipressin for injection

0.85 mg/vial

1 Single-Dose Vial

Discard Unused Portion

For Intravenous Use Only

Reconstitute with 5 mL of 0.9%
Sodium Chloride Injection, USP
before use